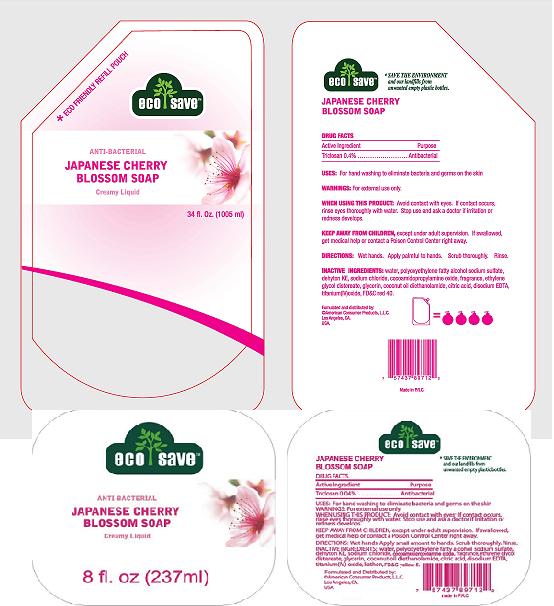 DRUG LABEL: ECOSAVE JAPANESE CHERRY BLOSSOM SOAP ANTIBACTERIAL HAND SOAP
NDC: 18018-504 | Form: KIT | Route: TOPICAL
Manufacturer: NINGBO CLEANER DAILY USED PRODUCTS
Category: otc | Type: HUMAN OTC DRUG LABEL
Date: 20091201

ACTIVE INGREDIENTS: TRICLOSAN .04 mL/100 mL; TRICLOSAN .04 mL/100 mL
INACTIVE INGREDIENTS: WATER; SODIUM CHLORIDE; CITRIC ACID MONOHYDRATE; EDETATE DISODIUM; WATER; SODIUM CHLORIDE; CITRIC ACID MONOHYDRATE; EDETATE DISODIUM

ECO-SAVE ANTI-BACTERIAL JAPANESE CHERRY BLOSSOM HAND SOAP

Drug Facts

Active Ingredients

Triclosan .04%

Purpose

Antibacterial

Warnings

For external use only

WHEN USING

Avoid contact with eyes. If contact occurs, rinse thoroughly with water. Stop use and ask a doctor if irritation or redness develops.

KEEP OUT OF REACH OF CHILDREN

Keep away from children, except under adult supervision. If swallowed, get medical help or contact a Posion Control Center right away.

DOSAGE AND ADMINISTRATION

Wet hands. Apply palmful to hands. Scrub thoroughly. Rinse.

Inactive Ingredients

water, polyoxyethylene fatty alcohol sodium sulfate,dehyton KE, sodium chloride, cocoamidopropylamine oxide, fragrance, ethylene glycol distereate, glycerin, coconut oil diethanolamide, citric acid, disodium EDTA,titanium IVoxide, FD AND C red 40

PACKAGE LABEL

artwork